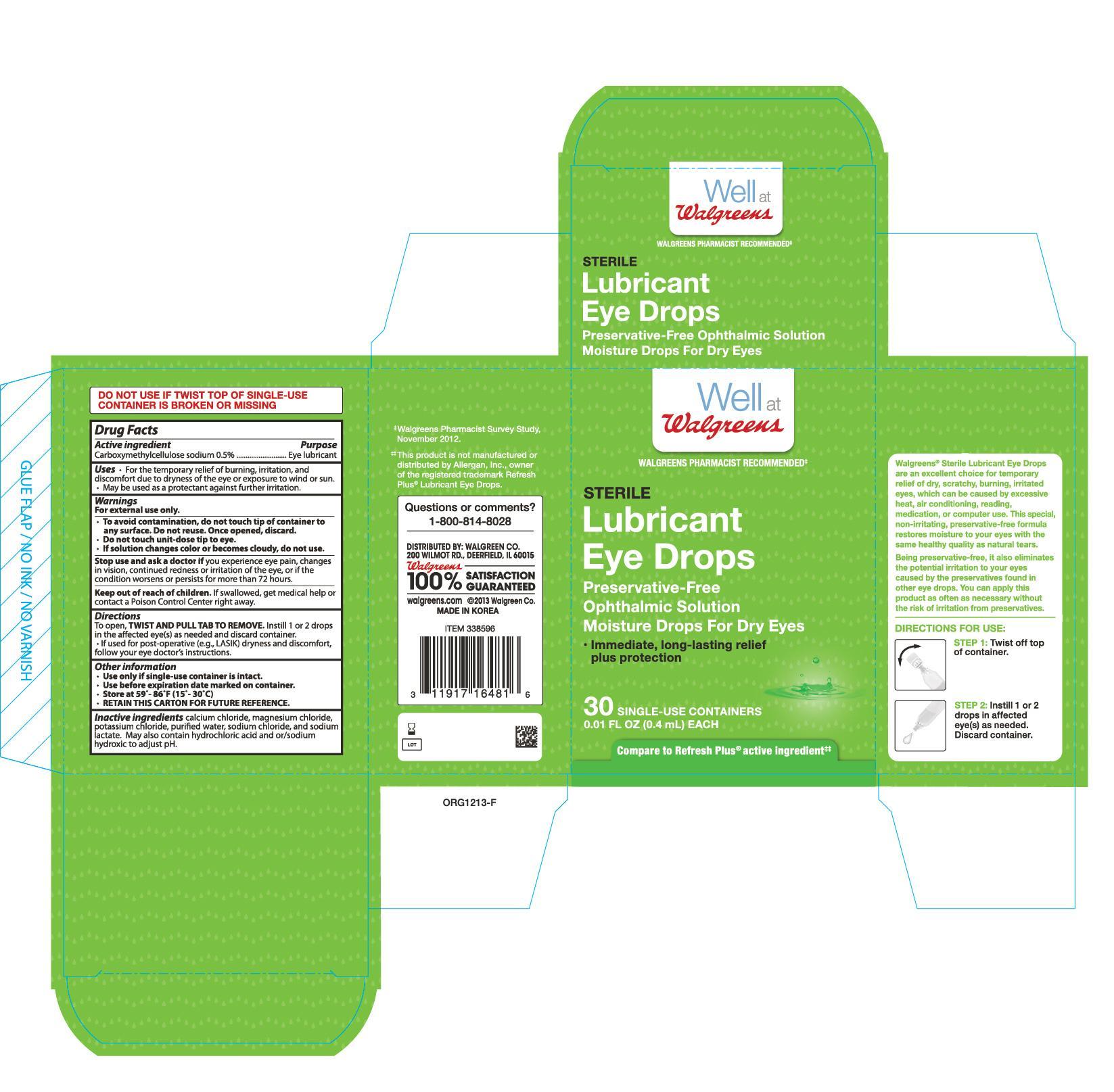 DRUG LABEL: Walgreen Sterile Lubricant Drops 30 Count
NDC: 0363-4816 | Form: SOLUTION/ DROPS
Manufacturer: Walgreen Company
Category: otc | Type: HUMAN OTC DRUG LABEL
Date: 20221215

ACTIVE INGREDIENTS: CARBOXYMETHYLCELLULOSE SODIUM 5 mg/1 mL
INACTIVE INGREDIENTS: MAGNESIUM CHLORIDE; POTASSIUM CHLORIDE; WATER; SODIUM CHLORIDE; SODIUM LACTATE; CALCIUM CHLORIDE

Walgreens Lubricant Eye Drops 30ct (NBE Refresh Plus) 338596

Active Ingredients Purpose

Carboxymethylcellulose sodium 0.5%................. Eye lubricant

Uses

- For the temporary relief of buring, irritation, and discomofort due to dryness of the eye or exposure to wind or sun
- May be used as a protectant against further irritation

Warnings

For external use only

When using this product

- do not touch tip of container to any surface to avoid contamination
- do not reuse
- once opened, discard
- do not use if this solution changes color or becomes cloudy
- remove contact lenses before using

Stop use and ask a doctor if

- you experience eye pain
- changes in vision occur
- continued redness or irritation of the eye lasts
- condition worsens or persists for more than 72 hours

PREGNANCY OR BREAST FEEDING

If pregnant or breast-feeding, ask a health professional before use.

Keep out of reach of children. If swallowed, get medical help or contact a Poison Control Center (1-800-222-1222) right away.

Directions

- to open, twis and pull tab to remove
- instill 1 or 2 drops in the affected eye(s) as needed
- children under 6 years of age: ask a doctor

Other information

- store between 15-30°C (59°-86°F)
- protect from light

Inactive ingredients

calcium chloride, hydrochloric acid, magnesium chloride, potassium chloride, purified water, sodium chloride, sodium hydroxide, sodium lactate

DOSAGE AND ADMINISTRATION

DISTRIBUTED BY:

WALGREEN CO.

200 WILMOT ROAD

DEERFIELD, IL 60015 USA